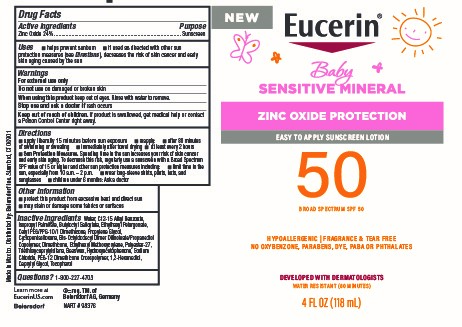 DRUG LABEL: Eucerin Baby Sensitive Mineral SPF 50 Sunscreen
NDC: 66800-4000 | Form: LOTION
Manufacturer: Beiersdorf Inc
Category: otc | Type: HUMAN OTC DRUG LABEL
Date: 20251231

ACTIVE INGREDIENTS: ZINC OXIDE 24 g/100 g
INACTIVE INGREDIENTS: WATER; BUTYLOCTYL SALICYLATE; CAPRYLYL GLYCOL; 1,2-HEXANEDIOL; ISOPROPYL PALMITATE; PEG-12 DIMETHICONE/PPG-20 CROSSPOLYMER; ALKYL (C12-15) BENZOATE; CETYL PEG/PPG-10/1 DIMETHICONE (HLB 2); BIS-OCTYLDODECYL DIMER DILINOLEATE/PROPANEDIOL COPOLYMER; HYDROXYACETOPHENONE; SODIUM CHLORIDE; TOCOPHEROL; CYCLOMETHICONE 5; ETHYLHEXYL METHOXYCRYLENE; TRIETHOXYCAPRYLYLSILANE; PROPYLENE GLYCOL; ETHYLHEXYL PELARGONATE; DIMETHICONE; POLYESTER-7; SYNTHETIC BEESWAX

Eucerin Baby Sensitive Mineral SPF 50 Sunscreen Lotion

Active ingredient

Zinc Oxide 24%

Purpose

Sunscreen

Uses

■ helps prevent sunburn

■ if used as directed with other sun protection measures (see Directions), decreases the risk of skin cancer and early skin aging caused by the sun

Warnings

For external use only

Do not useon damaged or broken skin

WHEN USING

When using this productkeep out of eyes. Rinse with water to remove.

Stop use and ask a doctor ifrash occurs

Keep out of reach of children.If product is swallowed, get medical help or contact a Poison Control Center right away.

Directions

■ apply liberally 15 minutes before sun exposure
■ reapply:
■ after 80 minutes of swimming or sweating
■ immediately after towel drying
■ at least every 2 hours
■ Sun Protection Measures.Spending time in the sun increases your risk of skin
cancer and early skin aging. To decrease this risk, regularly use a sunscreen
with a Broad Spectrum SPF value of 15 or higher and other sun protection
measures including:
■ limit time in the sun, especially from 10 a.m. – 2 p.m.
■ wear long-sleeve shirts, pants, hats, and sunglasses
■ children under 6 months: Ask a doctor

Other information

■ protect this product from excessive heat and direct sun

■ may stain or damage some fabrics or surfaces

Inactive ingredients

Water, C12-15 Alkyl Benzoate, Isopropyl Palmitate, Butyloctyl Salicylate, Ethylhexyl Pelargonate, Cetyl PEG/PPG-10/1 Dimethicone, Propylene Glycol, Cyclopentasiloxane, Bis-Octyldodecyl Dimer Dilinoleate/Propanediol Copolymer, Dimethicone, Ethylhexyl Methoxycrylene, Polyester-27, Triethoxycaprylylsilane, Beeswax, Hydroxyacetophenone, Sodium Chloride, PEG-12 Dimethicone Crosspolymer, 1,2-Hexanediol, Caprylyl Glycol, Tocopherol

Questions?

1-800-227-4703

PACKAGE LABEL

NEW

Eucerin®

Baby

Sensitive Mineral

Zinc Oxide Protection

Easy to apply Sunscreen Lotion

50Broad Spectrum SPF 50

Hyopallergenic | Fragrance & Tear Free

No Oxybenzone, Parabens, Dye, PABA or PHTHALATES

Developed with Dermatologists

4 FL OZ (118 mL)